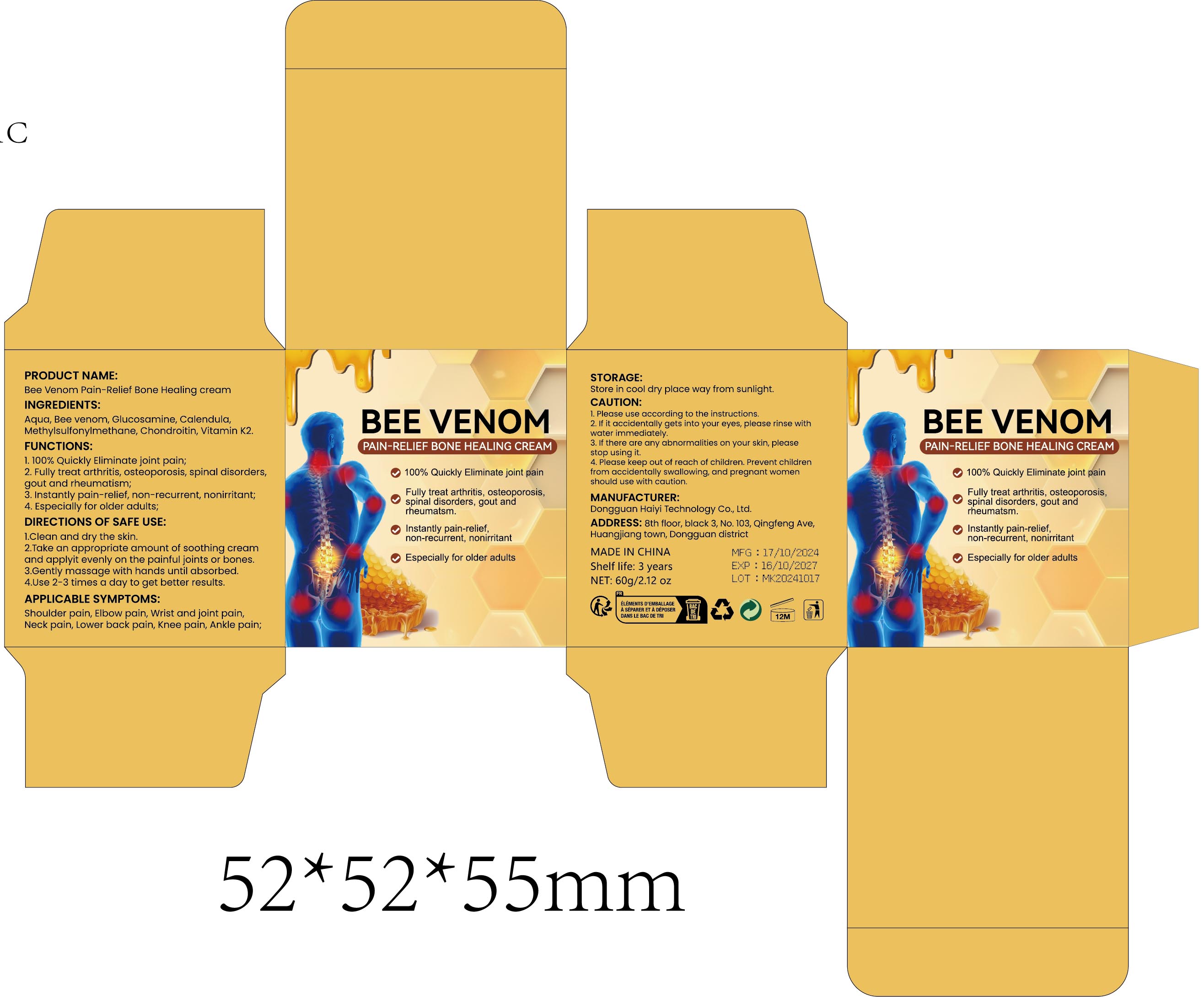 DRUG LABEL: Bee Venom Pain-Relief Bone Healing Cream
NDC: 84732-066 | Form: CREAM
Manufacturer: Dongguan Haiyi Technology Co.,Ltd.
Category: otc | Type: HUMAN OTC DRUG LABEL
Date: 20241025

ACTIVE INGREDIENTS: APIS MELLIFERA VENOM 1 mg/60 g
INACTIVE INGREDIENTS: WATER; CHONDROITIN SULFATE (BOVINE); CALENDULADIOL; MENAQUINONE 6; GLUCOSAMINE; DIMETHYL SULFOXIDE

Active ingredient

Bee venom

Inactive ingredient

Aqua, Glucosamine, calendula,Methylsulfonylmethane, Chondroitin, Vitamin K2.

Purpose section

1.100% Quickly Eliminate joint pain;

2. Fully treat arthritis, osteoporosis, spinal disorders,gout and rheumatism;

3. Instantly pain-relief, non-recurrent, nonirritant;

4. Especially for older adults,

Warning

1).For external use only, avoid directcontact with eyes, lf you feel any
discomfort, stop using itand wash it with plenty of water. In severe cases,
pleaseseek medical attention in time.
2). Not allowed to be used ondamaged skin,

stop use

This product may cause allergic reactions in asmall number of people.
lf youexperience any discomfort,please stop using it immediately.

not use

Not suitable for use by children, pregnantor breast feeding people.

OUT OF CHILDREN

KEEP THE PRODUCT OUT OF REACH OF CHILDREN to

HOW TO USE

1.Clean and dry the skin.

2.Take an appropriate amount of soothing creamand applyit evenly on the painful joints or bones.

3.Gently massage with hands until absorbed.

4.Use 2-3 times a day to get better results.

DOSAGE

Use 2-3 times a day to get better results.